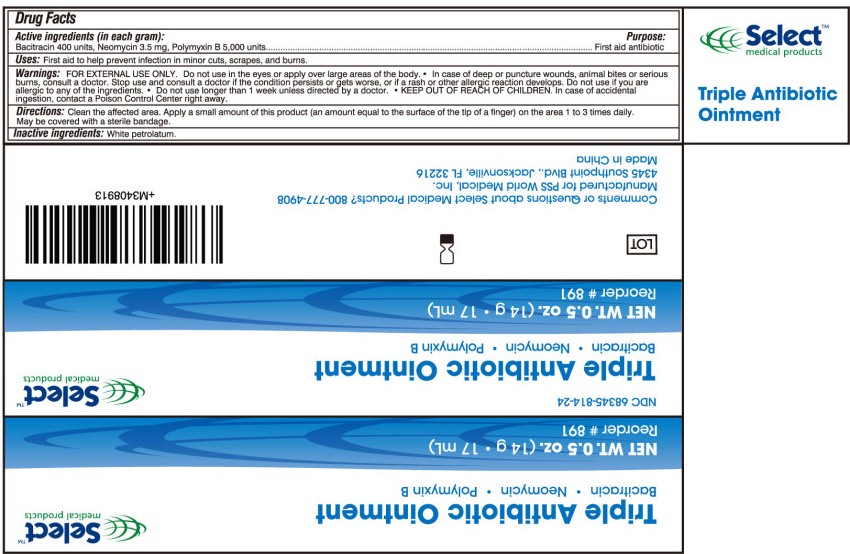 DRUG LABEL: Select Medical Products Triple Antibiotic
NDC: 68345-814 | Form: OINTMENT
Manufacturer: PSS WORLD MEDICAL, INC.
Category: otc | Type: HUMAN OTC DRUG LABEL
Date: 20100325

ACTIVE INGREDIENTS: BACITRACIN 400 [iU]/1 g; NEOMYCIN 3.5 mg/1 g; POLYMYXIN B 5000 [iU]/1 g
INACTIVE INGREDIENTS: PETROLATUM

Drug Facts

Warnings:

FOR EXTERNAL USE ONLY. Do not use in the eyes or apply over large areas of the body.

• In case of deep or puncture wounds, animal bites or serious burns, consult a doctor.

Stop use and consult a doctor if the condition persists or gets worse, or if a rash or other allergic reaction develops.

Do not use if you are allergic to any of the ingredients.

• Do not use longer than 1 week unless directed by a doctor.

• KEEP OUT OF REACH OF CHILDREN.

In case of accidental ingestion, contact a Poison Control Center right away.

Directions:

Clean the affected area.Apply a small amount of this product (an amount equal to the surface of the tip of a finger) on the area 1 to 3 times a day.
May be covered with a sterile bandage.

Inactive ingredients:

White petrolatum.

Comments or Questions about Select Medical Products? 800-777-4908

Manufactured for PSS World Medical, Inc.
4345 Southpoint Blvd., Jacksonville, FL32216
Made in China

Principal Display Panel - 0.5oz Tube Box

Select Medical Products™
NDC 68345-814-24
Triple Antibiotic Ointment
Bacitracin•Neomycin•Polymyxin B
NET WT. 0.5oz.(14g•17ml)
Reorder #891